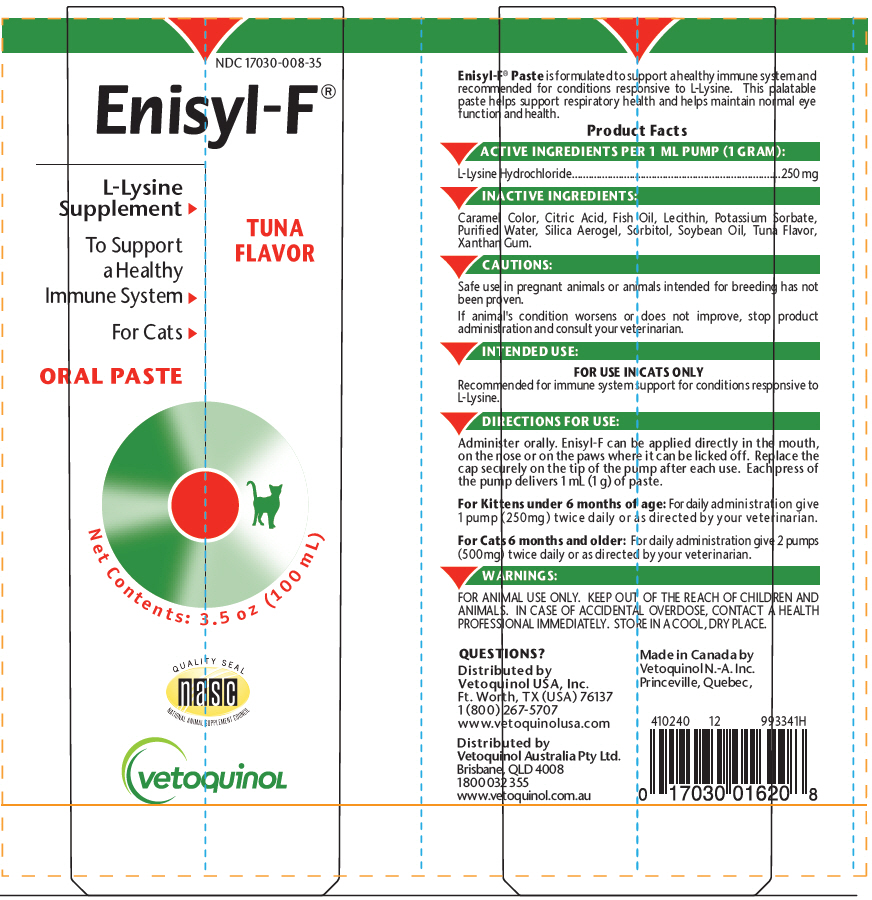 DRUG LABEL: ENISYL-F
NDC: 17030-008 | Form: PASTE
Manufacturer: Vetoquinol USA, Inc.
Category: animal | Type: OTC ANIMAL DRUG LABEL
Date: 20200506

ACTIVE INGREDIENTS: LYSINE HYDROCHLORIDE 250 mg/1 mL
INACTIVE INGREDIENTS: CITRIC ACID MONOHYDRATE; FISH OIL; LECITHIN, SOYBEAN; POTASSIUM SORBATE; WATER; SILICON DIOXIDE; SORBITOL; SOYBEAN OIL; XANTHAN GUM

Enisyl-F®

Enisyl-F® Paste is formulated to support a healthy immune system and recommended for conditions responsive to L-Lysine. This palatable paste helps support respiratory health and helps maintain normal eye function and health.

Product Facts

DESCRIPTION

ACTIVE INGREDIENTS PER 1 ML PUMP (1 GRAM):

L-Lysine Hydrochloride | 250 mg

INACTIVE INGREDIENTS:

Caramel Color, Citric Acid, Fish Oil, Lecithin, Potassium Sorbate, Purified Water, Silica Aerogel, Sorbitol, Soybean Oil, Tuna Flavor, Xanthan Gum.

PRECAUTIONS

CAUTIONS:

Safe use in pregnant animals or animals intended for breeding has not been proven.

If animal's condition worsens or does not improve, stop product administration and consult your veterinarian.

VETERINARY INDICATIONS

INTENDED USE:

FOR USE IN CATS ONLY

Recommended for immune system support for conditions responsive to L-Lysine.

DOSAGE AND ADMINISTRATION

DIRECTIONS FOR USE:

Administer orally. Enisyl-F can be applied directly in the mouth, on the nose or on the paws where it can be licked off. Replace the cap securely on the tip of the pump after each use. Each press of the pump delivers 1 mL (1 g) of paste.

For Kittens under 6 months of age: For daily administration give 1 pump (250mg) twice daily or as directed by your veterinarian.

For Cats 6 months and older: For daily administration give 2 pumps (500mg) twice daily or as directed by your veterinarian.

WARNINGS:

FOR ANIMAL USE ONLY. KEEP OUT OF THE REACH OF CHILDREN AND ANIMALS. IN CASE OF ACCIDENTAL OVERDOSE, CONTACT A HEALTH PROFESSIONAL IMMEDIATELY. STORE IN A COOL, DRY PLACE.

QUESTIONS?
Distributed by
Vetoquinol USA, Inc.
Ft. Worth, TX (USA) 76137
1 (800) 267-5707
www.vetoquinolusa.com

Distributed by
Vetoquinol Australia Pty Ltd.
Brisbane, QLD 4008
1 800 032 355
www.vetoquinol.com.au

Made in Canada by
Vetoquinol N.-A. Inc.
Princeville, Quebec,

410240 12 993341H

PRINCIPAL DISPLAY PANEL - 100 mL Tube Label

NDC 17030-008-35

Enisyl-F®

L-Lysine
Supplement ⯈

To Support
a Healthy
Immune System ⯈

For Cats ⯈

ORAL PASTE

TUNA
FLAVOR

Net Contents: 3.5 oz (100 mL)

QUALITY SEAL
nasc
NATIONAL ANIMAL SUPPLEMENT COUNCIL

vetoquinol